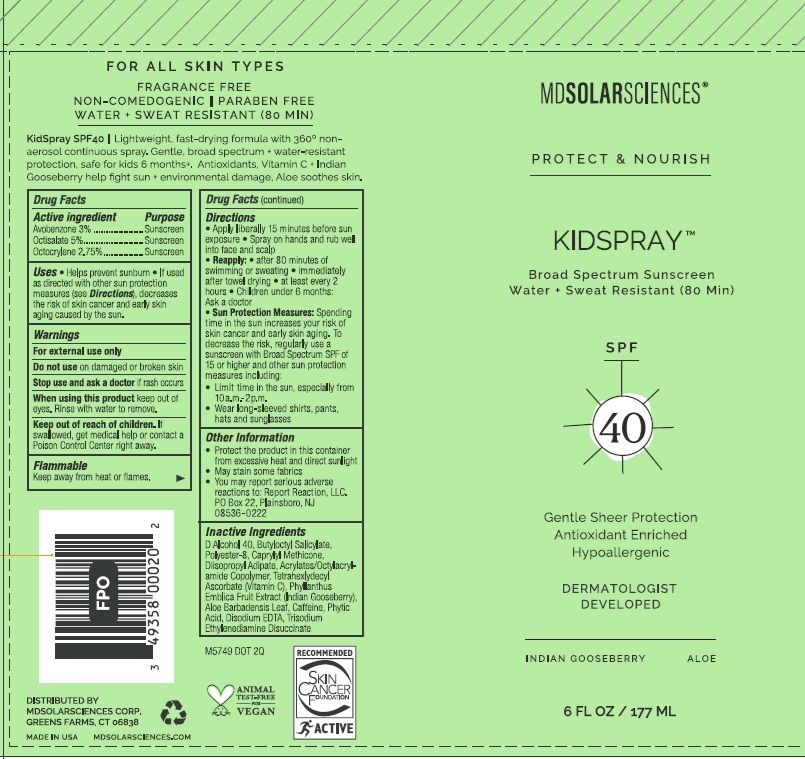 DRUG LABEL: Kidspray
NDC: 49358-001 | Form: SPRAY
Manufacturer: MDSolarSciences
Category: otc | Type: HUMAN OTC DRUG LABEL
Date: 20250605

ACTIVE INGREDIENTS: AVOBENZONE 30 mg/1 mL; OCTISALATE 50 mg/1 mL; OCTOCRYLENE 27.5 mg/1 mL
INACTIVE INGREDIENTS: ACRYLATES/OCTYLACRYLAMIDE COPOLYMER (75000 MW); EDETATE DISODIUM; BUTYLOCTYL SALICYLATE; ALCOHOL; POLYESTER-8 (1400 MW, CYANODIPHENYLPROPENOYL CAPPED); DIISOPROPYL ADIPATE; ALOE VERA LEAF; CAFFEINE; PHYTIC ACID; PHYLLANTHUS EMBLICA FRUIT; TETRAHEXYLDECYL ASCORBATE; TRISODIUM ETHYLENEDIAMINE DISUCCINATE

Kidspray
Broad Spectrum Sunscreen SPF 40

Drug Facts

ACTIVE INGREDIENT

Active Ingredients | Purpose
Avobenzone 3% | Sunscreen
Octisalate 5% | Sunscreen
Octocrylene 2.75% | Sunscreen

Uses

- Helps prevent sunburn
- If used as directed with other sun protection measures (see Directions), decreases the risk of skin cancer and early skin aging caused by the sun.

Warnings

For external use only

Do not use on damaged or broken skin

Stop use and ask a doctor if rash occurs.

When using this product keep out of eyes. Rinse with water to remove.

Keep out of reach of children. If swallowed, get medical help or contact a Poison Control Center right away.

Flammable

Keep away from heat or flames.

Directions

- Apply liberally 15 minutes before sun exposure
- Spray on hands and rub well into face and scalp
- Reapply:
  - After 80 minutes of swimming or sweating
  - Immediately after towel drying
  - At least every 2 hours
- Children under 6 months: Ask a doctor
- Sun Protection Measures:Spending time in the sun increases your risk of skin cancer and early skin aging. To decrease the risk, regularly use a sunscreen with Broad Spectrum SPF of 15 or higher and other sun protection measures including:
  - Limit time in the sun, especially from 10a.m. – 2p.m.
  - Wear long-sleeved shirts, pants, hats and sunglasses.

Other Information

- Protect the product in this container from excessive heat and direct sunlight
- May stain some fabrics
- You may report serious adverse reactions to Report Reaction, LLC. PO Box 22, Plainsboro, NJ 08536-0222

Inactive ingredients

SD Alcohol 40, Butyloctyl Salicylate, Polyester-8, Caprylyl Methicone, Diisopropyl Adipate, Acrylates/Octylacrylamide Copolymer, Tetrahexlydecyl Ascorbate (Vitamin C), Phyllanthus Emblica Fruit Extract (Indian Gooseberry), Aloe Barbadensis Leaf, Caffeine, Phytic Acid, Disodium EDTA, Trisodium Ethylenediamine Disuccinate

Distributed by:
MDSolarSciences Corp.
Greens Farms, CT 06838